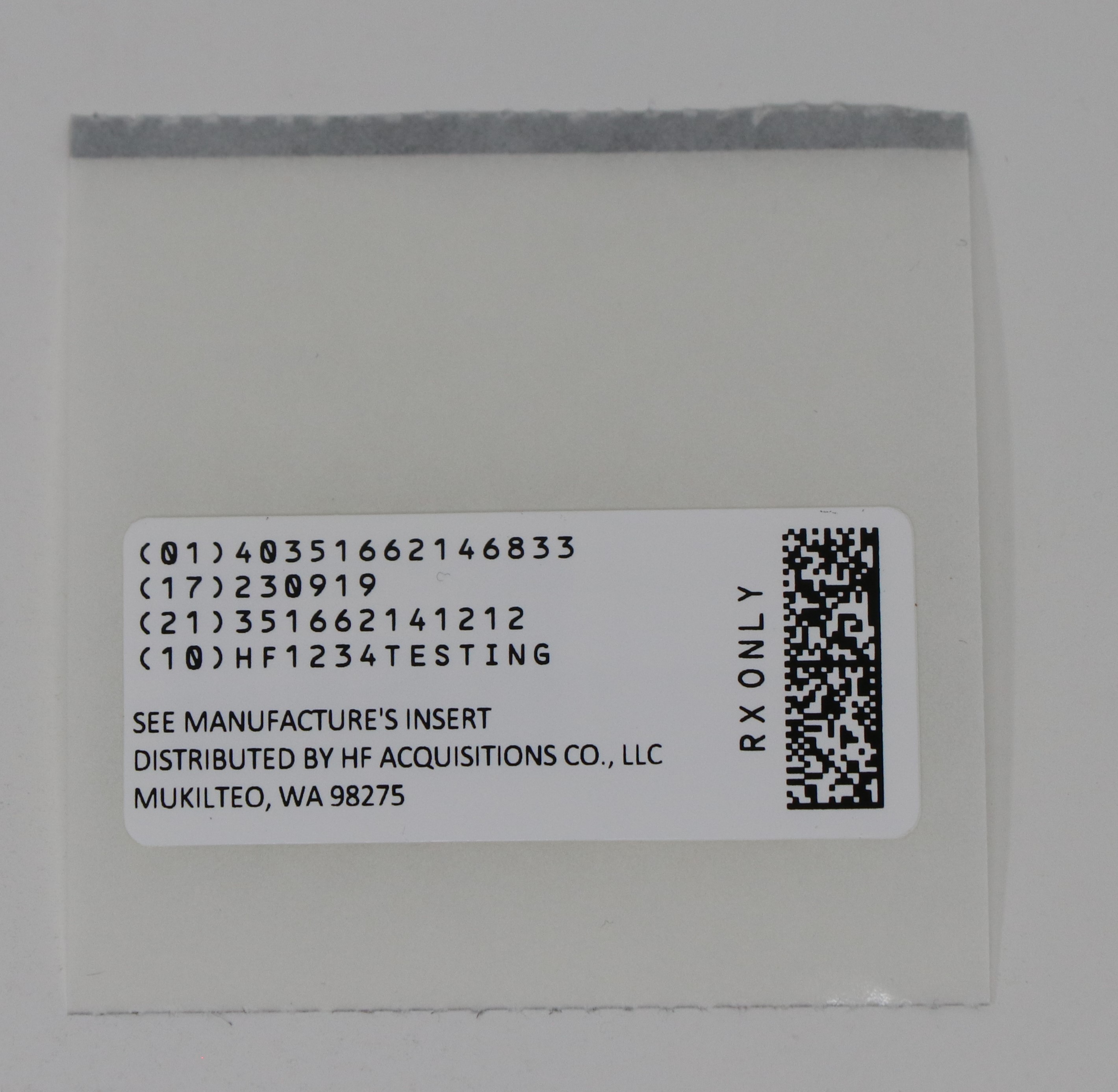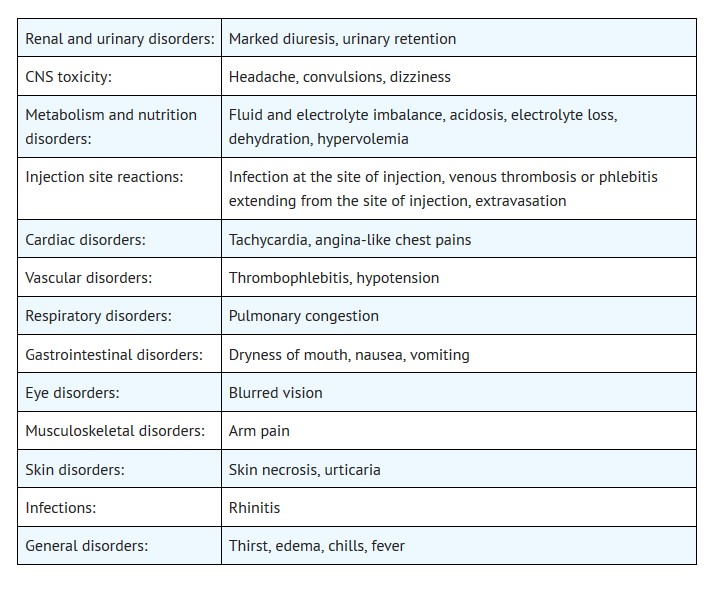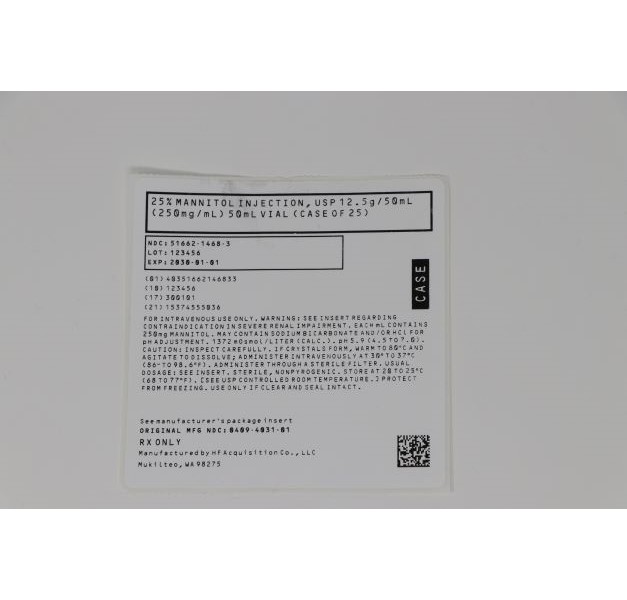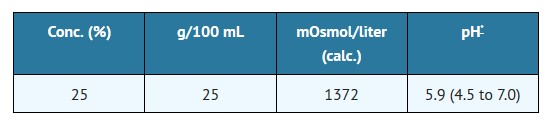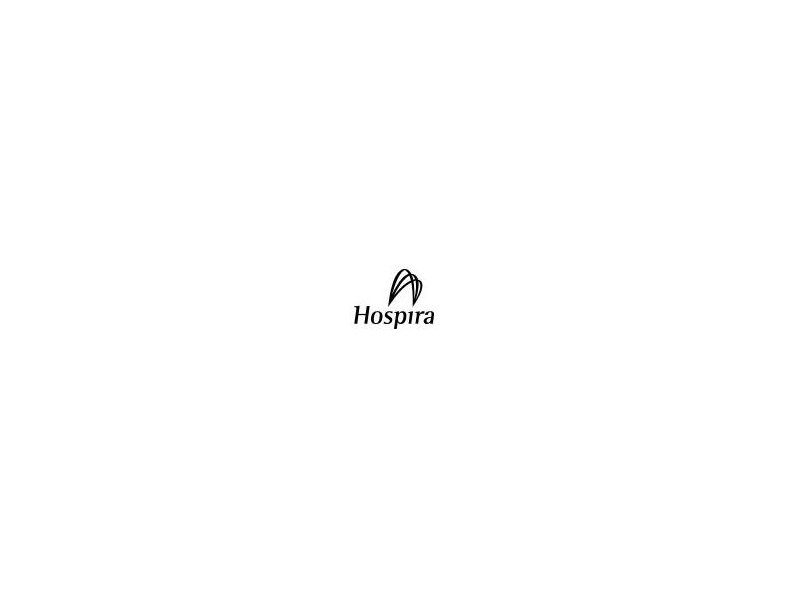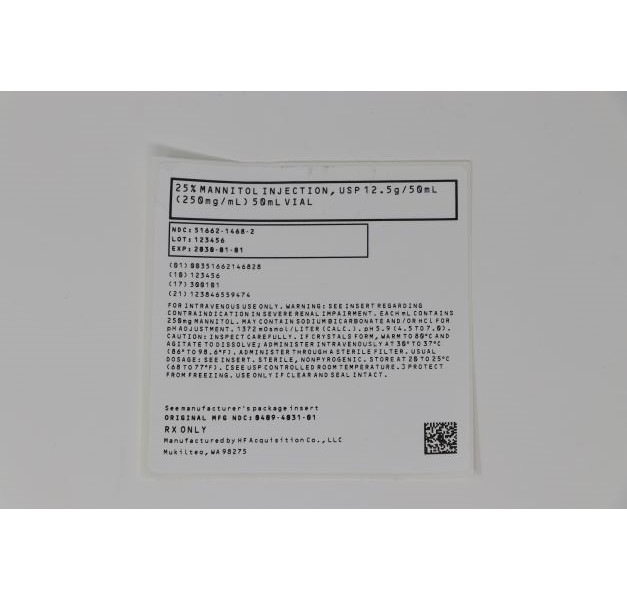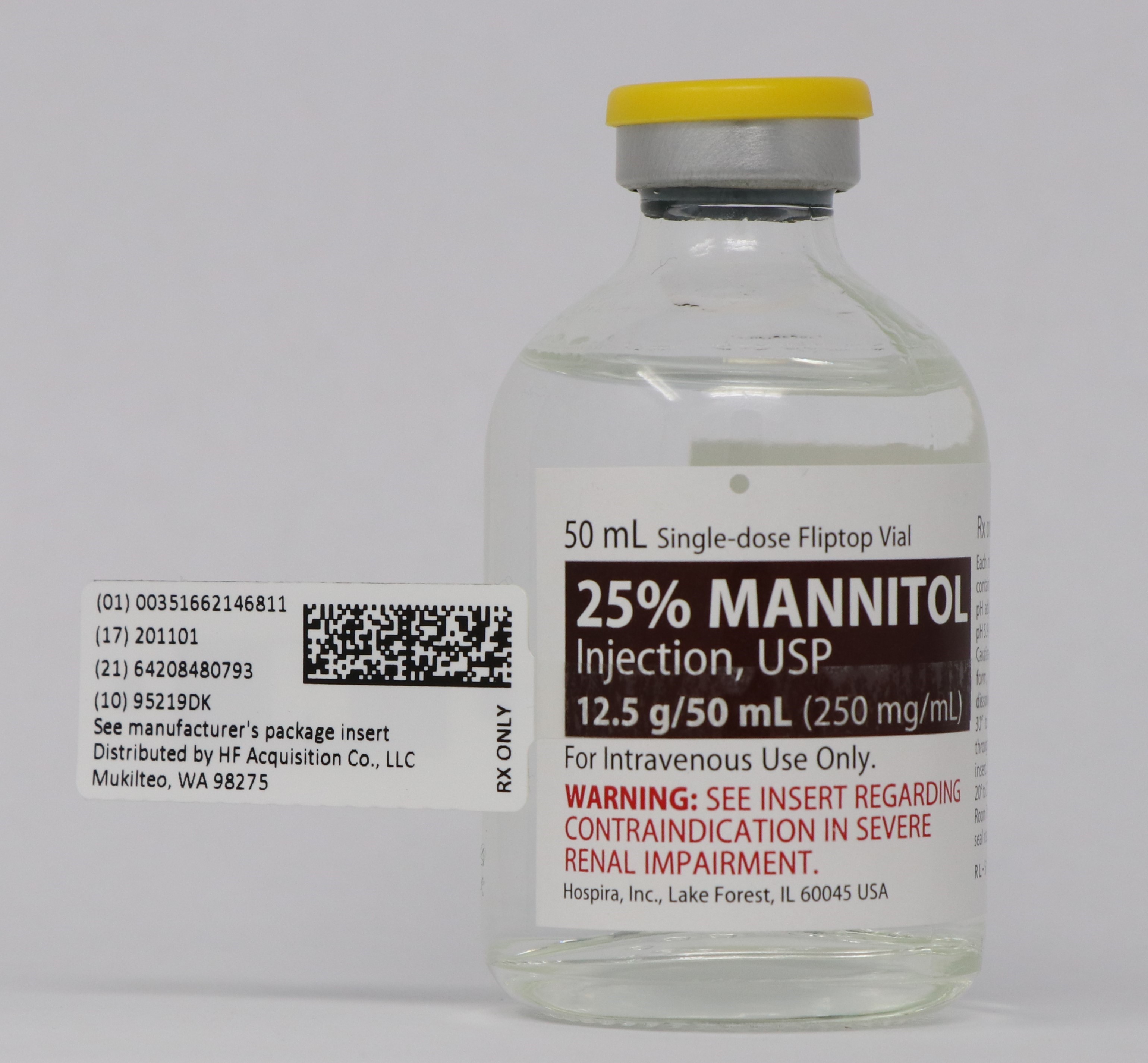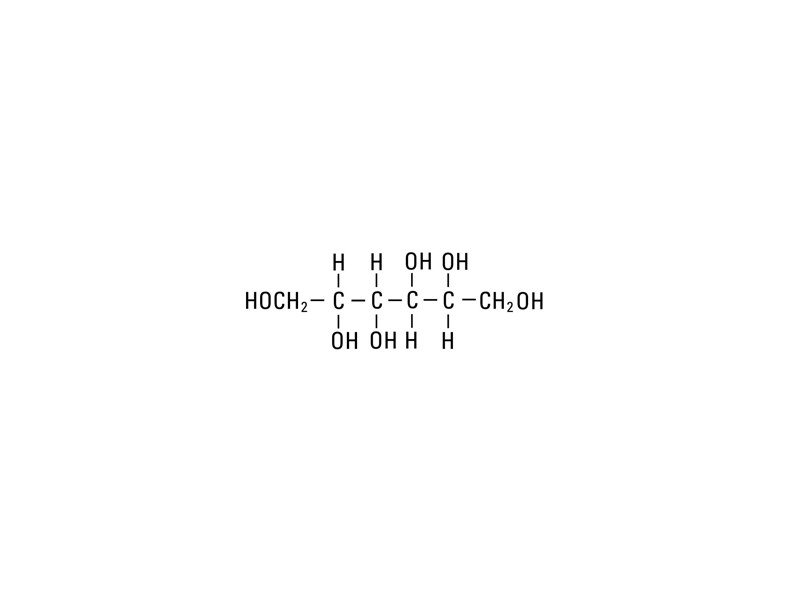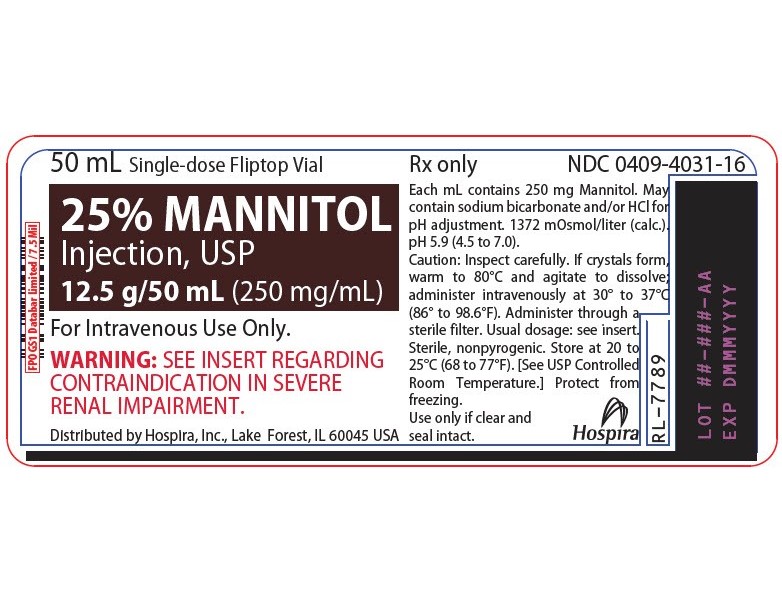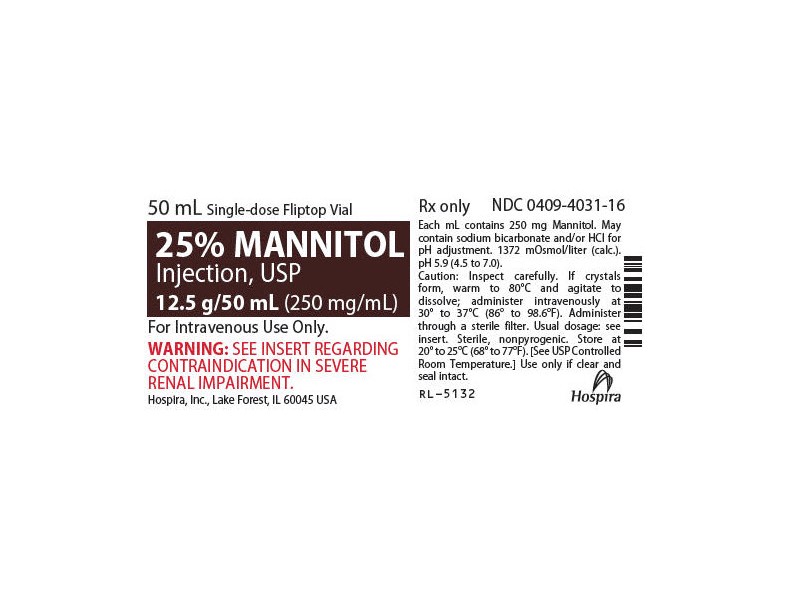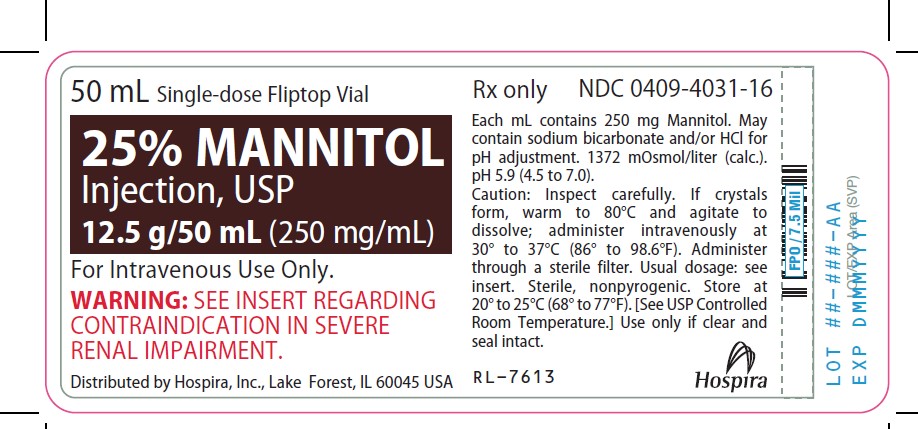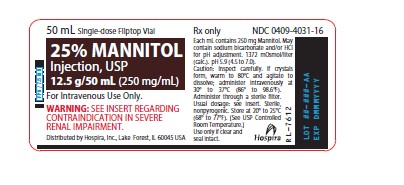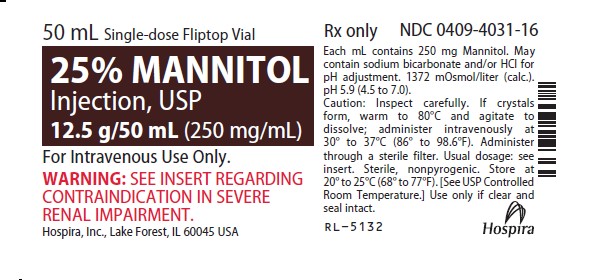 DRUG LABEL: MANNITOL
NDC: 51662-1468 | Form: INJECTION, SOLUTION
Manufacturer: HF Acquisition Co LLC, DBA HealthFirst
Category: prescription | Type: HUMAN PRESCRIPTION DRUG LABEL
Date: 20240127

ACTIVE INGREDIENTS: MANNITOL 12.5 g/50 mL
INACTIVE INGREDIENTS: SODIUM BICARBONATE; WATER; HYDROCHLORIC ACID

25% MANNITOL INJECTION, USP 12.5g/50mL (250mg/mL) 50mL VIAL

HIGHLIGHTS OF PRESCRIBING INFORMATION

These highlights do not include all the information needed to use MANNITOL INJECTION safely and effectively. See full prescribing information for MANNITOL INJECTION.
MANNITOL injection, for intravenous use
Initial U.S. Approval: 1964

INDICATIONS AND USAGE

Mannitol Injection is indicated for the following purposes in adults and pediatric patients.

Therapeutic Use

Reduction of intracranial pressure and brain mass. (1)
Reduction of high intraocular pressure. (1)

Diagnostic Use

Measurement of glomerular filtration rate. (1)

DOSAGE AND ADMINISTRATION

Administration Instructions (2-2.1):

For intravenous use only.
Do not add mannitol in whole blood for transfusion.

Recommended Dosage (2-2.2):

The dosage, concentration and rate of administration depend on the age, weight and condition of the patient.
Reduction of Intracranial Pressure and Brain Mass:
Adults: 0.25 to 2 g/kg body weight as a 15% to 25% solution administered over a period of 30 to 60 minutes
Pediatric patients: 1 to 2 g/kg body weight or 30 to 60 g/m2 body surface area over a period of 30 to 60 minutes.
Small or debilitated patients: 500 mg/kg
Reduction of Intraocular Pressure:
Adults: 0.25 to 2 g/kg body weight as a 15% to 25% solution administered over a period of 30 to 60 minutes
Pediatric patients: 1 to 2 g/kg body weight or 30 to 60 g/m2 body surface area over a period of 30 to 60 minutes
Small or debilitated patients: 500 mg/kg
Measurement of Glomerular Filtration Rate (GFR):
100 mL of a 20% solution (20 g) should be diluted with 180 mL of sodium chloride injection (normal saline) or 200 mL of a 10% solution (20 g) should be diluted with 80 mL of sodium chloride injection (normal saline). The resulting 280 mL of 7.2% solution is infused at a rate of 20 mL per minute.

DOSAGE FORMS AND STRENGTHS

Mannitol Injection, USP: 25% (250 mg/mL): 25 grams of mannitol, USP per 100 mL in a single-dose 50 mL fliptop vial (3)

CONTRAINDICATIONS

Well established anuria due to severe renal disease. (4)
Severe pulmonary congestion or frank pulmonary edema. (4)
Active intracranial bleeding except during craniotomy. (4)
Severe dehydration. (4)
Progressive heart failure or pulmonary congestion after institution of mannitol therapy. (4)

Do not administer to patients with a known hypersensitivity to mannitol. (4)

WARNINGS AND PRECAUTIONS

Renal Complications Including Renal Failure: Risk factors include pre-existing renal disease, conditions that put patients at risk for renal failure and concomitant use of nephrotoxic drugs or other diuretics. Avoid concomitant administration of nephrotoxic drugs or other diuretics with mannitol. (5-5.1, 8-8.6)
Fluid and Electrolyte Imbalances: Mannitol administration may obscure and intensify inadequate hydration or hypovolemia. Excessive loss of water and electrolytes may lead to serious imbalances, e.g., hypernatremia, hyponatremia. Accumulation of mannitol may intensify existing or latent congestive heart failure. Monitoring of cardiovascular status and electrolyte levels is recommended. (5-5.2)
Central Nervous System (CNS) Toxicity: Mannitol may increase cerebral blood flow and the risk of postoperative bleeding in neurosurgical patients. It may also worsen intracranial hypertension in children who develop a generalized cerebral hyperemia during the first 24 to 48 hours post injury. (5-5.3)
Monitoring: Discontinue mannitol if renal, cardiac or pulmonary status worsens, or CNS toxicity develops. (5-5.4)

ADVERSE REACTIONS

Most common adverse reactions are pulmonary congestion, fluid and electrolyte imbalance, acidosis, electrolyte loss, dryness of mouth, thirst, marked diuresis, urinary retention, edema, headache, blurred vision, convulsions, nausea, vomiting, rhinitis, arm pain, skin necrosis, thrombophlebitis, chills, dizziness, urticaria, dehydration, hypotension, tachycardia, fever and angina-like chest pains. (6)

To report SUSPECTED ADVERSE REACTIONS, contact Hospira, Inc. at 1-800-441-4100 or FDA at 1-800-FDA-1088 or www.fda.gov/medwatch.

DRUG INTERACTIONS

Nephrotoxic Drugs and Diuretics: May increase the risk of renal failure; avoid concomitant use. (7-7.1, 7-7.2)

See 17 for PATIENT COUNSELING INFORMATION.

Revised: 9/2019

1 INDICATIONS & USAGE

Mannitol Injection is indicated for the following purposes in adults and pediatric patients.

Therapeutic Use

Reduction of intracranial pressure and brain mass.
Reduction of high intraocular pressure.

Diagnostic Use

Measurement of glomerular filtration rate.

2 DOSAGE & ADMINISTRATION

2.1 Important Preparation and Administration Instructions

For intravenous use only. Do not administer intramuscularly or subcutaneously. Never add mannitol in whole blood for transfusion.

Do not administer unless solution is clear and container is undamaged. Discard unused portion. Do not administer 25% mannitol if the fliptop vial seal is not intact.

Additives may be incompatible. Consult with pharmacist, if available.

Do not place 25% Mannitol Injection in polyvinylchloride (PVC) bags; a white flocculent precipitate may form from contact with PVC surfaces. Parenteral drug products should be inspected visually for particulate matter and discoloration whenever container and solution permit.

2.2 Recommended Dosage

Reduction of Intracranial Pressure and Brain Mass

In adults a dose of 0.25 to 2 g/kg body weight as a 15% to 25% solution administered over a period of 30 to 60 minutes; pediatric patients 1 to 2 g/kg body weight or 30 to 60 g/m2 body surface area over a period of 30 to 60 minutes. In small or debilitated patients, a dose of 500 mg/kg may be sufficient. Careful evaluation must be made of the circulatory and renal reserve prior to and during administration of mannitol at the higher doses and rapid infusion rates. Careful attention must be paid to fluid and electrolyte balance, body weight, and total input and output before and after infusion of mannitol. Evidence of reduced cerebral spinal fluid pressure must be observed within 15 minutes after starting infusion.

Reduction of Intraocular Pressure

In adults a dose of 0.25 to 2 g/kg body weight as a 15% to 25% solution administered over a period of 30 to 60 minutes; pediatric patients 1 to 2 g/kg body weight or 30 to 60 g/m2 body surface area over a period of 30 to 60 minutes. In small or debilitated patients, a dose of 500 mg/kg may be sufficient. When used preoperatively, the dose should be given one to one and one-half hours before surgery to achieve maximal reduction of intraocular pressure before operation.

Measurement of Glomerular Filtration Rate (GFR)

100 mL of a 20% solution (20 g) should be diluted with 180 mL of sodium chloride injection (normal saline) or 200 mL of a 10% solution (20 g) should be diluted with 80 mL of sodium chloride injection (normal saline). The resulting 280 mL of 7.2% solution is infused at a rate of 20 mL per minute. The urine is collected by catheter for a specific period of time and analyzed for mannitol excreted in mg per minute. A blood sample is drawn at the start and at the end of the time period and the concentration of mannitol determined in mg/mL of plasma. GFR is the number of mL of plasma that must have been filtered to account for the amount excreted per minute in the urine. Normal clearance rates are approximately 125 mL/minute for men; 116 mL/minute for women.

3 DOSAGE FORMS AND STRENGTHS

Mannitol Injection, USP: 25% (250 mg/mL): 25 grams of mannitol, USP per 100 mL in a single-dose 50 mL fliptop vial

4 CONTRAINDICATIONS

Mannitol Injection is contraindicated in patients with:

Well established anuria due to severe renal disease.
Severe pulmonary congestion or frank pulmonary edema.
Active intracranial bleeding except during craniotomy.
Severe dehydration.
Progressive heart failure or pulmonary congestion after institution of mannitol therapy.

Do not administer to patients with a known hypersensitivity to mannitol.

5 WARNINGS AND PRECAUTIONS

5.1 Renal Complications Including Renal Failure

Renal complications, including irreversible renal failure have been reported in patients receiving mannitol.

Reversible, oliguric acute kidney injury (AKI) has occurred in patients with normal pretreatment renal function who received mannitol.

Osmotic nephrosis, a reversible vacuolization of the tubules of no known clinical significance, may proceed to severe irreversible nephrosis, so that the renal function must be closely monitored during mannitol infusion.

Patients with pre-existing renal disease, patients with conditions that put them at risk for renal failure, or those receiving potentially nephrotoxic drugs or other diuretics, are at increased risk for renal failure. Avoid concomitant administration of nephrotoxic drugs (e.g., aminoglycosides) or other diuretics with mannitol [see Drug Interactions (7)].

If urine output declines during mannitol infusion, the patient's clinical status should be closely reviewed and mannitol infusion suspended if necessary.

5.2 Fluid and Electrolyte Imbalances

The obligatory diuretic response following rapid infusion of 25% mannitol may further aggravate pre-existing hemoconcentration. Excessive loss of water and electrolytes may lead to serious imbalances. With continued administration of mannitol, loss of water in excess of electrolytes can cause hypernatremia. Electrolyte measurements, including sodium and potassium are therefore of vital importance in monitoring the infusion of mannitol.

The shift of sodium-free intracellular fluid into the extracellular compartment following mannitol infusion may lower serum sodium concentration and aggravate pre-existing hyponatremia.

By sustaining diuresis, mannitol administration may obscure and intensify inadequate hydration or hypovolemia.

Accumulation of mannitol may result in overexpansion of the extracellular fluid which may intensify existing or latent congestive heart failure.

The cardiovascular status of the patient should be carefully evaluated before rapidly administering mannitol since sudden expansion of the extracellular fluid may lead to fulminating congestive heart failure.

5.3 Central Nervous System (CNS) Toxicity

Mannitol injection may increase cerebral blood flow and the risk of postoperative bleeding in neurosurgical patients.

Mannitol may increase cerebral blood flow and worsen intracranial hypertension in children who develop generalized cerebral hyperemia during the first 24 to 48 hours post injury.

5.4 Monitoring

Serum sodium and potassium should be carefully monitored during mannitol administration.

If an adverse reaction does occur, discontinue the infusion, evaluate the patient, institute appropriate therapeutic counter measures and save the remainder of the fluid for examination if deemed necessary.

Electrolyte-free mannitol solutions should not be given conjointly with blood. If it is essential that blood be given simultaneously, at least 20 mEq of sodium chloride should be added to each liter of mannitol solution to avoid pseudoagglutination.

When exposed to low temperatures, solutions of mannitol may crystallize. If crystals are observed, the container should be warmed to redissolve, then cooled to body temperature before administering [see How Supplied/Storage and Handling (16)]. When infusing 25% mannitol, the administration set should include a filter. Do not infuse mannitol solution if crystals are present.

6 ADVERSE REACTIONS

The following adverse reactions associated with the use mannitol were identified in clinical studies or postmarketing reports. Because some of these reactions were reported voluntarily from a population of uncertain size, it is not always possible to reliably estimate their frequency or establish a causal relationship to drug exposure.

7 DRUG INTERACTIONS

7.1 Nephrotoxic Drugs

Patients receiving potentially nephrotoxic drugs are at increased risk for renal failure. Avoid concomitant administration of nephrotoxic drugs (e.g., aminoglycosides) with mannitol [see Warnings and Precautions (5)].

7.2 Diuretics

Pateints receiving other diuretics are at increased risk for renal failure. Avoid concomitant administration of other diuretics with mannitol [see Warnings and Precautions (5)].

8 USE IN SPECIFIC POPULATIONS

8.1 Pregnancy

Risk Summary

There are no well-controlled studies in pregnant women that establish developmental toxicity related to the use of mannitol injection. Mannitol crosses the placenta and may cause fluid shifts that could potentially result in adverse effects in the fetus (see Data). The available data do not establish the presence or absence of developmental toxicity related to the use of mannitol.

There are limited animal data in the published literature. The effects of mannitol on embryo-fetal development have not been evaluated; however, fluid shifts occurred in animal studies in response to maternal infusion of mannitol.

Mannitol injection should be given to a pregnant woman only if clearly needed.

The estimated background risk of major birth defects and miscarriage for the indicated population is unknown. All pregnancies have a background risk of birth defect, loss, or other adverse outcomes. In the U.S. general population, the estimated background risk of major birth defects and miscarriage in clinically recognized pregnancies is 2–4% and 15–20%, respectively.

Data

Human Data

Published literature reports the presence of mannitol in amniotic fluid when mannitol is administered to pregnant women during the third trimester of pregnancy.

8.2 Lactation

Risk Summary

Lactation studies have not been conducted with mannitol. It is not known whether this drug is excreted in human milk. Mannitol injection should be administered to lactating women only if clearly indicated. Studies assessing the effects of mannitol injection in breastfed children have not been performed. Studies to assess the effect of mannitol on milk production or excretion have not been performed.

The developmental and health benefits of breastfeeding should be considered along with the mother's clinical need for mannitol and any potential adverse effects on the breastfed child from mannitol or from the underlying maternal condition.

8.5 Geriatric Use

Mannitol is known to be substantially excreted by the kidney, and the risk of adverse reactions to this drug may be greater in elderly patients with impaired renal function. Evaluate the renal, cardiac and pulmonary status of the patient and correct fluid and electrolyte imbalances prior to administration of mannitol [see Warnings and Precautions (5)].

8.6 Renal Impairment

Patients with pre-existing renal disease, patients with conditions that put them at high risk for renal failure, or those receiving potentially nephrotoxic drugs or other diuretics, are at increased risk of renal failure with administration of mannitol. Evaluate the renal, cardiac and pulmonary status of the patient and correct fluid and electrolyte imbalances prior to administration of mannitol [see Warnings and Precautions (5)].

10 OVERDOSAGE

Too rapid infusion of large amounts of mannitol will cause a shift of intracellular water into the extracellular compartment resulting in cellular dehydration and overexpansion of the intravascular space with hyponatremia, congestive heart failure and pulmonary edema. Repeated doses should not be given to patients with persistent oliguria as this can produce a hyperosmolar state and precipitate congestive heart failure and pulmonary edema due to volume overload. Dosage must be carefully monitored and adjusted in accordance with the clinical situation to avoid the consequences of overdosage [see Contraindications (4), Warnings and Precautions (5), Dosage and Administration (2)].

11 DESCRIPTION

Mannitol Injection, USP is a sterile, nonpyrogenic solution of mannitol in water for injection available in a concentration of 25% in a fliptop vial for administration by intravenous infusion only.

The content and characteristics are as follows:

The solution contains no bacteriostat, antimicrobial agent or added buffer (except for pH adjustment) and is intended only as a single-dose injection. When smaller doses are required, the unused portion should be discarded.

Mannitol Injection, USP is a parenteral obligatory osmotic diuretic.

Mannitol, USP is chemically designated D-mannitol (C6H14O6), a white crystalline powder or free-flowing granules freely soluble in water. It has the following structural formula:

*
May contain sodium bicarbonate and/or hydrochloric acid for pH adjustment.

25 25 1372 5.9 (4.5 to 7.0)

Water for Injection, USP is chemically designated H2O.

12 CLINICAL PHARMACOLOGY

12.1 Mechanism of Action

Mannitol, when administered intravenously, exerts its osmotic diuretic effect as a solute of relatively small molecular size largely confined to the extracellular space. Mannitol hinders tubular reabsorption of water and enhances excretion of sodium and chloride by elevating the osmolarity of the glomerular filtrate.

By increasing the osmotic pressure of plasma and the extracellular space, intravenously administered mannitol will induce the movement of intracellular water to the extracellular and vascular spaces. This action underlies the role of mannitol in reducing intracranial pressure, intracranial edema, and intraocular pressure.

12.3 Pharmacokinetics

Distribution

Mannitol distributes largely to the extracellular space within 20 to 40 minutes after intravenous administration. The plasma half-life for this distribution phase is 0.16 hour. The volume of distribution of mannitol is approximately 17 L in adults.

Elimination

In subjects with normal renal function, the total clearance is 87 to 109 mL/minute. The elimination half-life of mannitol is 0.5 to 2.5 hours

Metabolism

Only a relatively small amount of the mannitol dose is metabolized after intravenous administration to healthy subjects.

Excretion

Approximately 80% of a 100 g dose appears in the urine in 3 hours. The drug is freely filtered by the glomeruli, with less than 10% tubular reabsorption; it is not secreted by tubular cells.

Specific Populations

Patients with Renal Impairment

In patients with renal impairment, the elimination half-life of mannitol is prolonged. In a published study, in patients with renal impairment including acute renal failure and end stage renal failure, the elimination half-life of mannitol was estimated at about 36 hours, based on serum osmolarity. In patients with renal impairment on dialysis, the elimination half-life of mannitol was reduced to 6 and 21 hours during hemodialysis and peritoneal dialysis, respectively.

13 NONCLINICAL TOXICOLOGY

13.1 Carcinogenesis, Mutagenesis, Impairment of Fertility

Studies with Mannitol Injection have not been performed to evaluate carcinogenic potential, mutagenic potential or effects on fertility.

16 HOW SUPPLIED/STORAGE AND HANDLING

Mannitol Injection, USP is supplied in single-dose containers as follows:

25% MANNITOL INJECTION, USP is supplied in the following dosage forms.
NDC 51662-1468-1
25% MANNITOL INJECTION, USP 12.5g/50mL (250mg/mL) 50mL VIAL

NDC 51662-1468-2
25% MANNITOL INJECTION, USP 12.5g/50mL (250mg/mL) 50mL VIAL, 1 VIAL PER POUCH

NDC 51662-1468-3
25% MANNITOL INJECTION, USP 12.5g/50mL (250mg/mL) 50mL VIAL, 1 VIAL PER POUCH, 25 POUCHES PER CASE

HF Acquisition Co LLC, DBA HealthFirst
Mukilteo, WA 98275

NOTE: Crystals may form in mannitol solutions especially if the solutions are chilled. To dissolve the crystals, warm the bottle in hot water at 80°C and periodically shake vigorously. 25% Mannitol Injection, USP may be autoclaved at 121°C for 20 minutes at 15 psi. Remove cover from fliptop vial and cleanse stopper with antiseptic before use. Cool to body temperature or less before administering. When infusing 25% mannitol concentrations, the administration set should include a filter.

Protect from freezing. Store at 20 to 25°C (68 to 77°F). [See USP Controlled Room Temperature.]

INSTRUCTlONS FOR USE

Remove cover and cleanse stopper with antiseptic before use.

17 PATIENT COUNSELING INFORMATION

Inform patients or caregivers of the following risks of Mannitol Injection:

Renal Complications Including Renal Failure [see Warnings and Precautions (5.1)].
Fluid and Electrolyte Imbalances [see Warnings and Precautions (5.2)]
CNS Toxicity [see Warnings and Precautions (5.3)]

SPL UNCLASSIFIED

Distributed by Hospira, Inc., Lake Forest, IL 60045 USA

LAB-1227-1.1

PRINCIPAL DISPLAY PANEL - VIAL LABEL OPT. 1

PRINCIPAL DISPLAY PANEL - VIAL LABEL OPT. 2

PRINCIPAL DISPLAY PANEL - VIAL LABEL OPT. 3

PRINCIPAL DISPLAY PANEL - VIAL LABEL OPT. 4

PRINCIPAL DISPLAY PANEL - SERIALIZED VIAL LABELING

PRINCIPAL DISPLAY PANEL - NDC 51662-1468-2 POUCH LABELING

NDC 51662-1468-2 POUCH LABELING

VIAL LABEL

PRINCIPAL DISPLAY PANEL - NDC 51662-1468-3 CASE LABELING

CASE LABELING NDC 51662-1468-3

51662-1468-3 SERIALIZED RFID LABELING